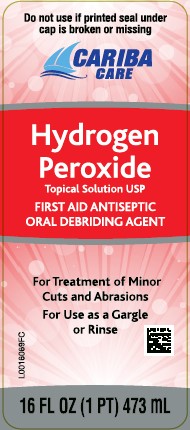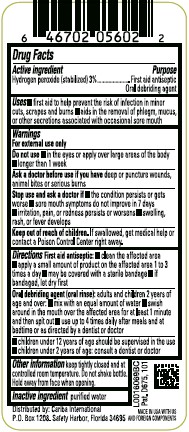 DRUG LABEL: Hydrogen Peroxide
NDC: 67860-871 | Form: SOLUTION
Manufacturer: Cariba International
Category: otc | Type: HUMAN OTC DRUG LABEL
Date: 20260129

ACTIVE INGREDIENTS: HYDROGEN PEROXIDE 30 mg/1 mL
INACTIVE INGREDIENTS: WATER

Cariba 871.001/871AA
Hydrogen Peroxide 3%

Active ingredient

Hydrogen peroxide (stabilized) 3%

Purpose

First Aid Antiseptic

Oral debriding agent

Uses

- first aid to help prevent the risk of infection in minor cuts, scrapes and burns
- aids in the removal of phlegm, mucus, or other secretions associated with occasional sore mouth

Warnings

For external use only

Do Not Use

- in the eyes or apply over large areas of the body
- longer than 1 week

Ask a doctor before use if you have

deep or pucture wounds, animal bites or serious burns

Stop Use and ask a doctor if

- the condition persists or gets worse
- sore mouth symptoms do not improve in 7 days
- irritation, pain, or redess persists or worsens
- swelling, rash, or fever develops

Keep out of reach of children.

If swallowed, get medical help or contact a Poison Control Center right away.

Directions

First Aid antiseptic:

- clean the affected area
- apply a small amount of product on the affected area 1 to 3 times a day
- may be coverd with a sterile bandage
- if bandaged, let dry first

Oral debriding agent (oral rinse): adults, children over 2 years of age:

- mix with an equal amount of water
- swish around in the mouth over the affected area for at least 1 minure, then spit out
- use up to 4 times daily after meals and at bedtime or as directed by a dentist or doctor

- children under 12 years of age should be supervised in the use
- children under 2 years of age: consult a dentist, doctor

Other information

Keep tightly closed and at controlled room temperature. Do not shake bottle. Hold away from face when opening.

Inactive ingredient

purified water

ADVERSE REACTION

Distributed by: Cariba International

P.O. Box 1208 Safety Harbor, Florida 34695

MADE IN USA WITH US AND FOREIGN COMPONENTS

Pat. D675, 101

principal display panel

Do not use if printed seal under cap is broken or missing

CARIBA CARE

HYDROGEN PEROXIDE

TOPICAL SOLUTION USP

FIRST AID ANTISEPTIC

ORAL DEBRIDING AGENT

For Treatment of Minor Cuts and Abrasions

For Use as a Gargle or Rinse

16 FL OZ (1 PT) 473 mL